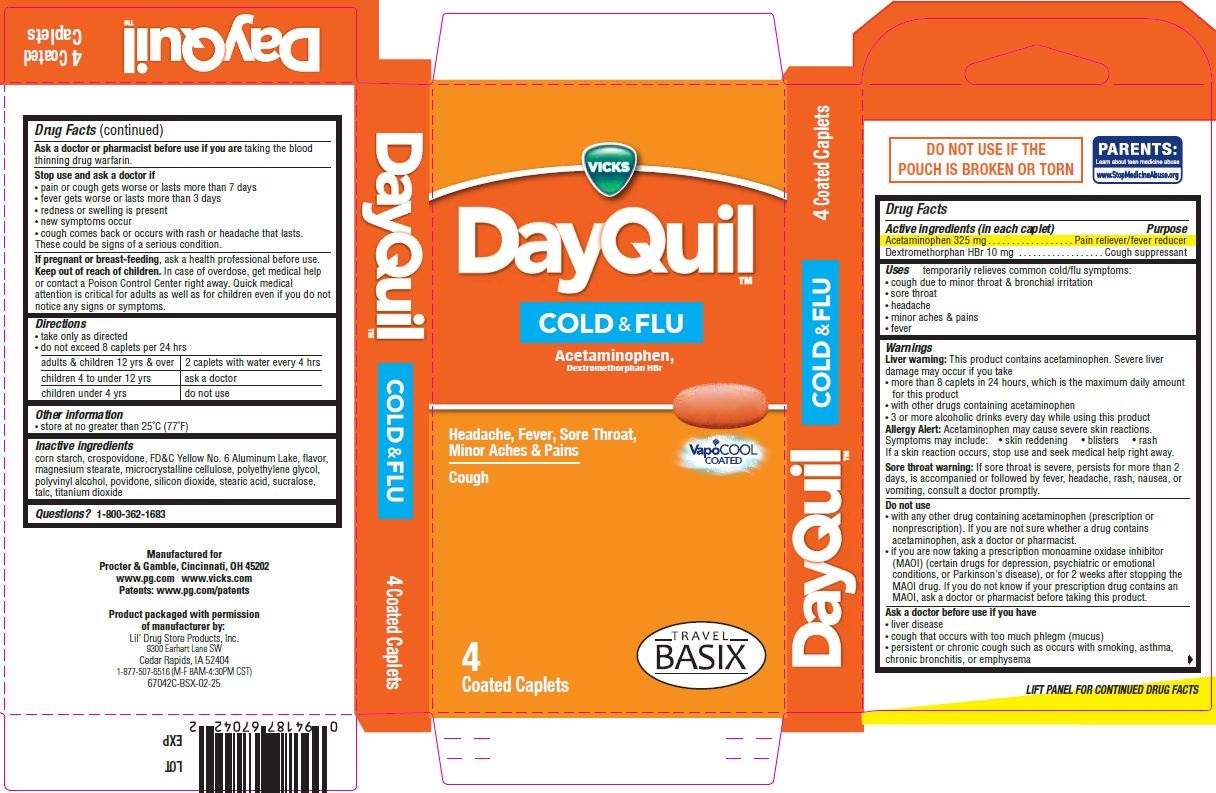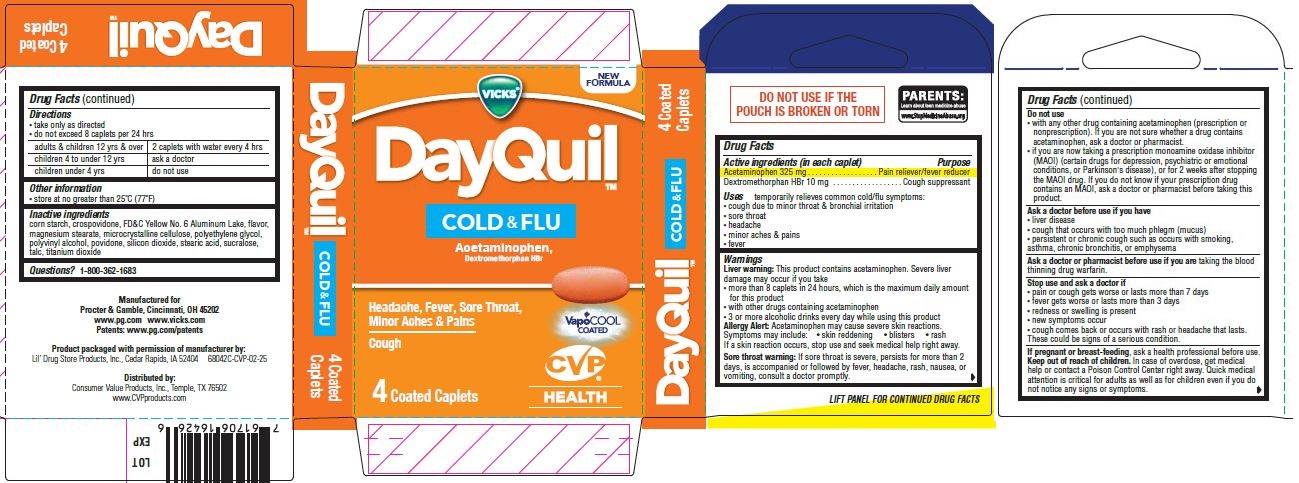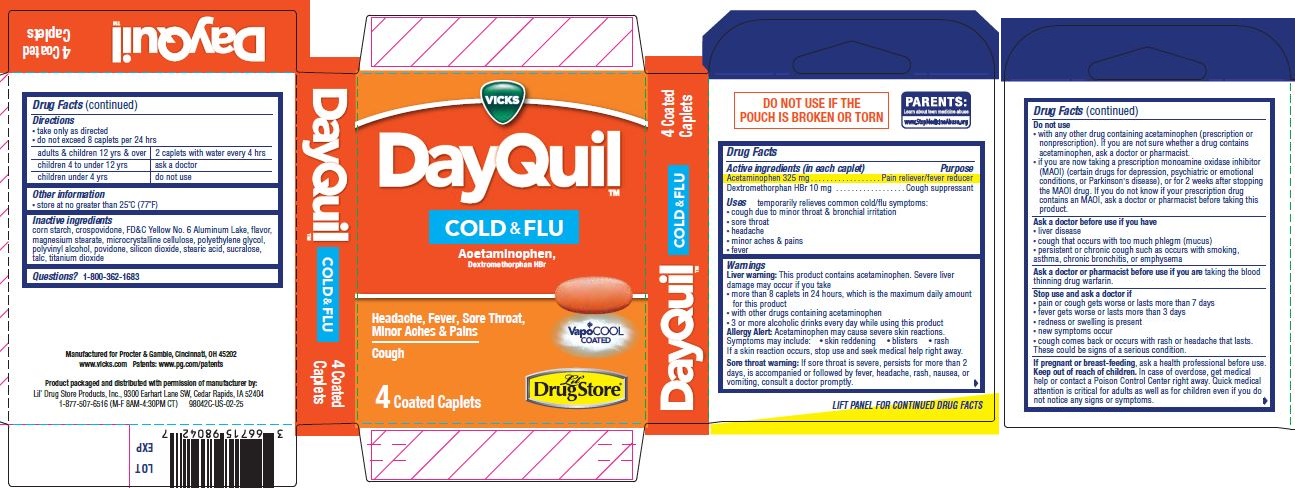 DRUG LABEL: DayQuil Cold and Flu w/VapoCOOL, 4ct (PE-free), BSX
NDC: 66715-6204 | Form: TABLET, COATED
Manufacturer: Lil' Drug Store Products, Inc.
Category: otc | Type: HUMAN OTC DRUG LABEL
Date: 20250620

ACTIVE INGREDIENTS: DEXTROMETHORPHAN HYDROBROMIDE 10 mg/1 1; ACETAMINOPHEN 325 mg/1 1
INACTIVE INGREDIENTS: MICROCRYSTALLINE CELLULOSE; POLYETHYLENE GLYCOL, UNSPECIFIED; POLYVINYL ALCOHOL, UNSPECIFIED; FD&C YELLOW NO. 6 ALUMINUM LAKE; POVIDONE, UNSPECIFIED; STEARIC ACID; SUCRALOSE; TITANIUM DIOXIDE; STARCH, CORN; CROSPOVIDONE; SILICON DIOXIDE; TALC; MAGNESIUM STEARATE

DayQuil™Cold & Flu w/VapoCOOL, 4ct (PE-free), Lil' Drug Store®
DayQuil™Cold & Flu w/VapoCOOL, 4ct (PE-free), CVP®
DayQuil™Cold & Flu w/VapoCOOL, 4ct (PE-free), BSX

Active ingredients (in each caplet)

Acetaminophen 325 mg

Dextromethorphan HBr 10 mg

Purpose

Pain reliever/fever reducer

Cough suppressant

Uses

temporarily relieves common cold/flu symptoms:

- cough due to minor throat & bronchial irritation
- sore throat
- headache
- minor aches & pains
- fever

Warnings

Liver warning

This product contains acetaminophen. Severe liver damage may occur if you take

- more than 8 caplets in 24 hours, which is the maximum daily amount for this product
- with other drugs containing acetaminophen
- 3 or more alcoholic drinks every day while using this product

Allergy alert

Acetaminophen may cause severe skin reactions.
Symptoms may include:

- skin reddening
- blisters
- rash

If a skin reaction occurs, stop use and seek medical help right away.

Sore throat warning

If sore throat is severe, persists for more than 2 days, is accompanied or followed by fever, headache, rash, nausea, or
vomiting, consult a doctor promptly.

Do not use

- with any other drug containing acetaminophen (prescription or nonprescription). If you are not sure whether a drug contains acetaminophen, ask a doctor or pharmacist.
- if you are now taking a prescription monoamine oxidase inhibitor (MAOI) (certain drugs for depression, psychiatric or emotional conditions, or Parkinson's disease), or for 2 weeks after stopping the MAOI drug. If you do not know if your prescription drug contains an MAOI, ask a doctor or pharmacist before taking this product.

Ask a doctor before use if you have

- liver disease
- cough that occurs with too much phlegm (mucus)
- persistent or chronic cough such as occurs with smoking, asthma, chronic bronchitis, or emphysema

Ask a doctor or pharmacist before use if you aretaking the blood thinning drug warfarin.

Stop use and ask a doctor if

- pain or cough gets worse or lasts more than 7 days
- fever gets worse or lasts more than 3 days
- redness or swelling is present
- new symptoms occur
- cough comes back or occurs with rash or headache that lasts.

These could be signs of a serious condition.

If pregnant or breast-feeding,ask a health professional before use.

Keep out of reach of children.In case of overdose, get medical help or contact a Poison Control Center right away. Quick medical
attention is critical for adults as well as for children even if you do not notice any signs or symptoms.

Directions

- take only as directed
- do not exceed 8 caplets per 24 hrs

adults & children 12 yrs & over | 2 caplets with water every 4 hrs
children 4 to under 12 yrs | ask a doctor
children under 4 yrs | do not use

Other information

- store at no greater than 25°C (77°F)

Inactive ingredients

corn starch, crospovidone, FD&C Yellow No. 6 Aluminum Lake, flavor, magnesium stearate, microcrystalline cellulose, polyethylene glycol, polyvinyl alcohol, povidone, silicon dioxide, stearic acid, sucralose, talc, titanium dioxide

Questions?

Questions?1-800-362-1683

DayQuil™Cold & Flu w/VapoCOOL, 4ct (PE-free), Lil' Drug Store®

VICKS

DayQuil™

COLD & FLU

Acetaminophen,

Dextromethorphan HBr

[caplet image]

Headache, Fever, Sore Throat,

Minor Aches & Pains

Cough

Vapo Cool

COATED

4 Coated Caplets

[Lil' Drug Store®logo]

DayQuil™Cold & Flu w/VapoCOOL, 4ct (PE-free), CVP®HEALTH

VICKS

DayQuilTM

COLD & FLU

Acetaminophen,

Dextromethorphan HBr

[caplet image]

Headache, Fever, Sore Throat,

Minor Aches & Pains

Cough

VapoCool

COATED

4 Coated Caplets

[CVP®HEALTH logo]

DayQuil™Cold & Flu w/VapoCOOL, 4ct (PE-free), Travel BASIX

VICKS

DayQuil™

COLD & FLU

Acetaminophen,

Dextromethorphan HBr

[caplet image]

Headache, Fever, Sore Throat,

Minor Aches & Pains

Cough

VapoCool

COATED

4 Coated Caplets

[Travel BASIX logo]